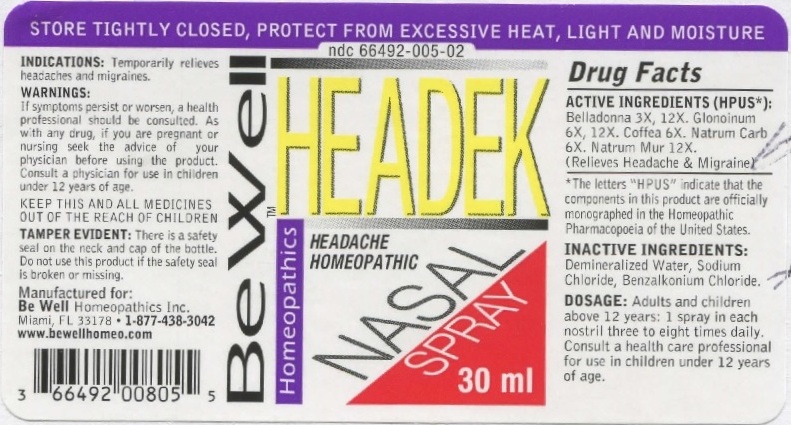 DRUG LABEL: Headek Nasal
NDC: 66492-005 | Form: SPRAY
Manufacturer: Be Well Medical dba Richard Clement Nutrition y Be Well Homeopathics
Category: homeopathic | Type: HUMAN OTC DRUG LABEL
Date: 20211229

ACTIVE INGREDIENTS: ATROPA BELLADONNA 3 [hp_X]/30 mL; NITROGLYCERIN 6 [hp_X]/30 mL; ARABICA COFFEE BEAN 6 [hp_X]/30 mL; SODIUM CARBONATE 6 [hp_X]/30 mL; SODIUM CHLORIDE 12 [hp_X]/30 mL
INACTIVE INGREDIENTS: WATER; BENZALKONIUM CHLORIDE

Headek Nasal Spray

ACTIVE INGREDIENT

ACTIVE INGREDIENTS (HPUS*): Belladonna 3X, 12X. Glonoinum 6X, 12X. Coffea 6X. Natrum Carb 6X. Natrum Mur 12X. (Relieves Headache & Migraine)

*The letters "HPUS" indicate that the components in the product are officially monographed in the Homeopathic Pharmacopeia of the United States.

INDICATIONS: Temporarily relieves headaches and migraines.

WARNINGS

WARNINGS: If symptoms persist or worsen, a health professional should be consulted. As with any drug, if you are pregnant or nursing seek the advice of your physician before using this product. Consult a physician for use in children under 12 years of age.

KEEP OUT OF REACH OF CHILDREN

Keep this and all medicines out of the reach of children.

DOSAGE AND ADMINISTRATION

DOSAGE: Adults and children above 12 years: 1 spray in each nostril three to eight times daily. Consult a health care professional for use in children under 12 years of age.

OTHER SAFETY INFORMATION

TAMPER EVIDENT: There is a safety seal on the neck and cap of the bottle. Do not use this product if the safety seal is broken or missing.

INACTIVE INGREDIENT

INACTIVE INGREDIENTS: Demineralized Water, Sodium Chloride, Benzalkonium Chloride.

QUESTIONS

Manufactured for: Be Well Homeopathics Inc. Miami, FL 33178 • 1-877-438-3042

www.bewellhomeo.com

PACKAGE LABEL

NDC 66492-005-02

Be Well Homeopathics

HEADEK NASAL SPRAY

30ml

PURPOSE

Headache/Migraines